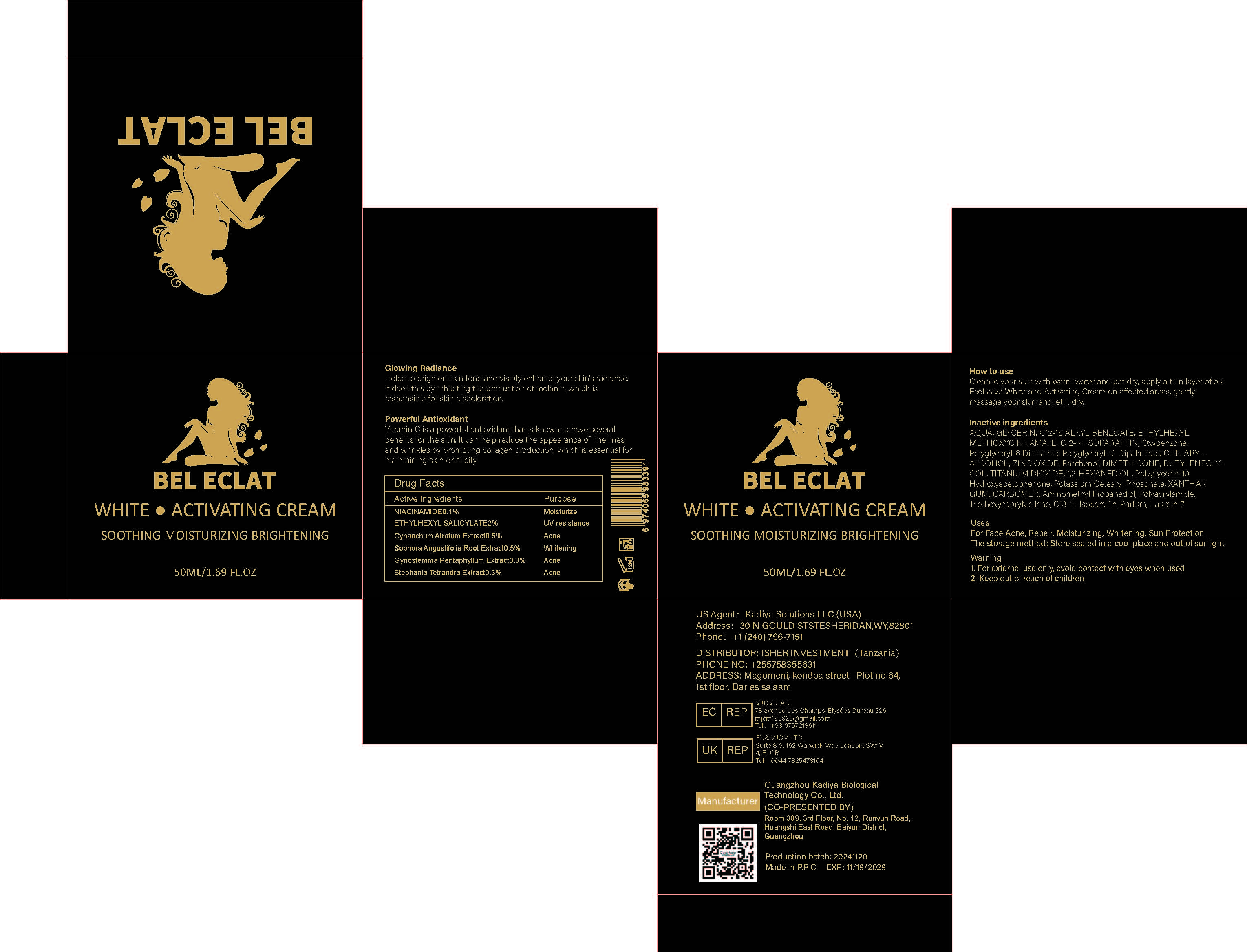 DRUG LABEL: WHITEACTIVATINGCREAM
NDC: 84423-074 | Form: CREAM, AUGMENTED
Manufacturer: Guangzhou Kadiya Biotechnology Co., Ltd.
Category: otc | Type: HUMAN OTC DRUG LABEL
Date: 20250218

ACTIVE INGREDIENTS: GYNOSTEMMA PENTAPHYLLUM WHOLE 0.15 g/50 mL; STEPHANIA TETRANDRA WHOLE 0.15 g/50 mL; ETHYLHEXYL SALICYLATE 1 g/50 mL; SOPHORA FLAVESCENS ROOT 0.25 g/50 mL; NIACINAMIDE 0.05 g/50 mL; VINCETOXICUM ATRATUM WHOLE 0.25 g/50 mL
INACTIVE INGREDIENTS: CETEARYL PHOSPHATE; CARBOMER; AMINOMETHYL PROPANEDIOL; 1,3-BUTYLENEGLYCOL DIMETHACRYLATE; C12-15 ALKYL BENZOATE; AQUA; CETEARYL ALCOHOL; TITANIUM DIOXIDE; PANTHENOL; TRIETHOXYCAPRYLYLSILANE; C13-14 ISOPARAFFIN; C12-14 ISOPARAFFIN; POLYGLYCERIN-10; HYDROXYACETOPHENONE; POLYACRYLAMIDE (10000 MW); LAURETH-7; BHT; DIMETHICONE; POLYGLYCERYL-6 DISTEARATE; ZINC OXIDE; GLYCERIN; POLYGLYCERYL-10 DIPALMITATE; 1,2-HEXANEDIOL; XANTHAN GUM; OXYBENZONE

PURPOSE

For Face Acne, Repair, Moisturizing, Whitening, Sun Protection

INACTIVE INGREDIENT

AQUA，GLYCERIN，C12-15 ALKYL BENZOATE，ETHYLHEXYL METHOXYCINNAMATE，C12-14 ISOPARAFFIN，Oxybenzone，Polyglyceryl-6 Distearate，Polyglyceryl-10 Dipalmitate，CETEARYL ALCOHOL，ZINC OXIDE，Panthenol，DIMETHICONE，BUTYLENEGLYCOL，TITANIUM DIOXIDE，1,2-HEXANEDIOL，Polyglycerin-10，Hydroxyacetophenone，Potassium Cetearyl Phosphate，XANTHAN GUM，CARBOMER，Aminomethyl Propanediol，Polyacrylamide，Triethoxycaprylylsilane，C13-14 Isoparaffin，Parfum，Laureth-7

Warning.
1、For external use only, avoid contact with eyes when used
2、Keep out of reach of children

INACTIVE INGREDIENT

Glowing RadianceHelps to brighten skin tone and visibly enhance your skin's radiance.t does this bv inhibitino the nroduction ot melanin. which eresponsible for skin discoloration.

DOSAGE AND ADMINISTRATION

Cleanse your skin with warm water and pat dry, apply a thin layer of our Exclusive White and Activating Cream on affected areas, gently massage your skin and let it dry

KEEP OUT OF REACH OF CHILDREN SECTION

Active Ingredients
NIACINAMIDE0.1%
ETHYLHEXYL SALICYLATE2%
Cynanchum Atratum Extract0.5%
Sophora Angustifolia Root Extract0.5%
Gynostemma Pentaphyllum Extract0.3%
Stephania Tetrandra Extract0.3%

INDICATIONS AND USAGE

Cleanse your skin with warm water and pat dry apply a thin layer ofour Exclusive White and Activating Cream on affected areas, gently massage your skin and let it dry

PACKAGE LABEL

Active Ingredients
NIACINAMIDE0.1%
ETHYLHEXYL SALICYLATE2%
Cynanchum Atratum Extract0.5%
Sophora Angustifolia Root Extract0.5%
Gynostemma Pentaphyllum Extract0.3%
Stephania Tetrandra Extract0.3%

Uses：
For Face Acne, Repair, Moisturizing, Whitening, Sun Protection
The storage method：
Store sealed in a cool place and out of sunlight

Warning.
1、For external use only, avoid contact with eyes when used
2、Keep out of reach of children

Inactive ingredients：
AQUA，GLYCERIN，C12-15 ALKYL BENZOATE，ETHYLHEXYL METHOXYCINNAMATE，C12-14 ISOPARAFFIN，Oxybenzone，Polyglyceryl-6 Distearate，Polyglyceryl-10 Dipalmitate，CETEARYL ALCOHOL，ZINC OXIDE，Panthenol，DIMETHICONE，BUTYLENEGLYCOL，TITANIUM DIOXIDE，1,2-HEXANEDIOL，Polyglycerin-10，Hydroxyacetophenone，Potassium Cetearyl Phosphate，XANTHAN GUM，CARBOMER，Aminomethyl Propanediol，Polyacrylamide，Triethoxycaprylylsilane，C13-14 Isoparaffin，Parfum，Laureth-7